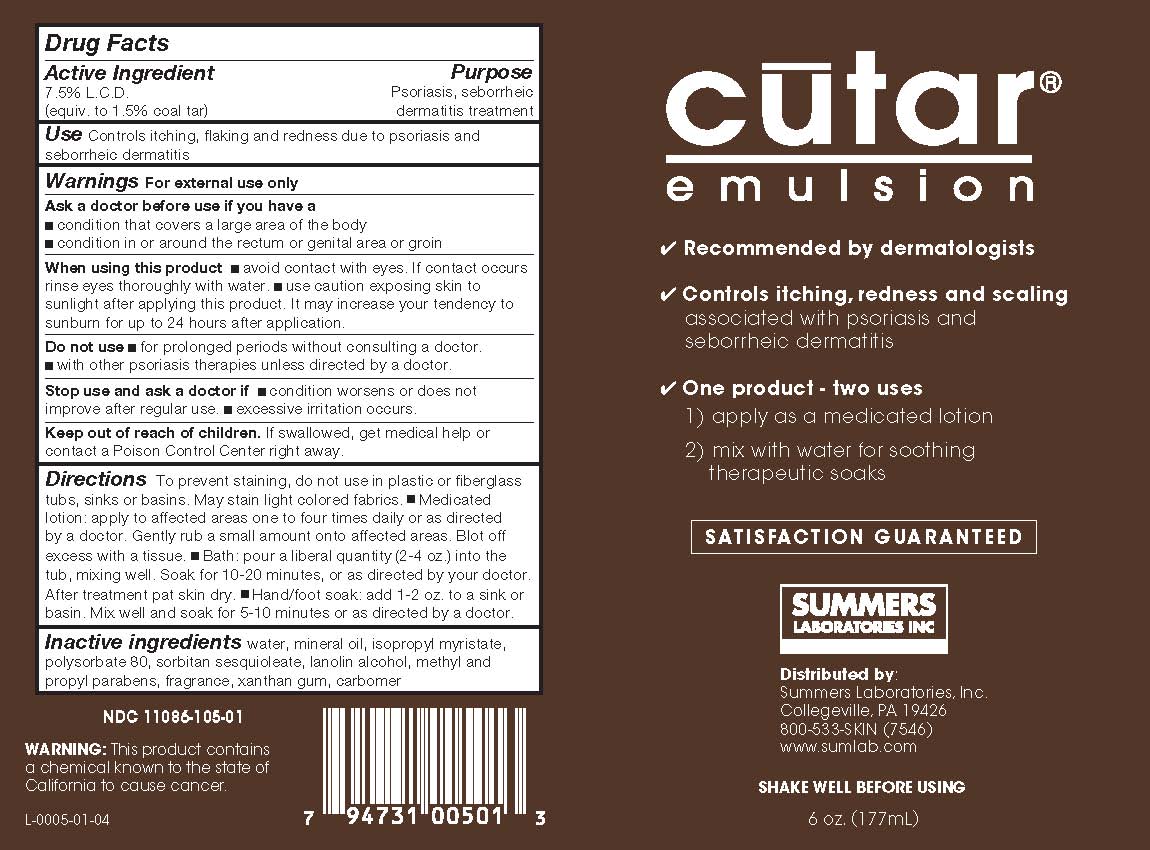 DRUG LABEL: CUTAR
NDC: 11086-105 | Form: LOTION
Manufacturer: Summers Laboratories Inc
Category: otc | Type: HUMAN OTC DRUG LABEL
Date: 20231009

ACTIVE INGREDIENTS: COAL TAR 1.5 g/100 mL
INACTIVE INGREDIENTS: WATER; MINERAL OIL; ISOPROPYL MYRISTATE; POLYSORBATE 80; SORBITAN SESQUIOLEATE; LANOLIN ALCOHOLS; METHYLPARABEN; PROPYLPARABEN; XANTHAN GUM; CARBOMER HOMOPOLYMER TYPE C (ALLYL PENTAERYTHRITOL CROSSLINKED)

SUMMERS LABS (as PLD) - CUTAR (11086-105)

ACTIVE INGREDIENT

7.5% L.C.D. (EQUIVALENT TO 1.5% COAL TAR)

PURPOSE

PSORIASIS, SEBORREIC DERMATITIS TREATMENT

USE

- CONTROLS ITCHING, FLAKING AND REDNESS DUE TO PSORIASIS AND SEBORRHEIC DERMATITIS

WARNINGS

FOR EXTERNAL USE ONLY

ASK A DOCTOR BEFORE USE IF YOU HAVE

- CONDITION THAT COVERS A LARGE AREA OF THE BODY
- CONDITION IN OR AROUND THE RECTUM, GENITAL AREA OR GROIN

WHEN USING THIS PRODUCT

- AVOID CONTACT WITH EYES. IF CONTACT OCCURS, RINSE EYES THOROUGHLY WITH WATER
- USE CAUTION IN EXPOSING SKIN TO SUNLIGHT AFTER APPLYING THIS PRODUCT. IT MAY INCREASE YOUR TENDENCY TO SUNBURN FOR UP TO 24 HOURS AFTER APPLICATION

DO NOT USE

- FOR PROLONGED PERIODS WITHOUT CONSULTING A DOCTOR
- WITH OTHER FORMS OF PSORIASIS THERAPY UNLESS DIRECTED TO DO SO BY A DOCTOR

STOP USE AND ASK A DOCTOR IF

- CONDITION WORSENS OR DOES NOT IMPROVE AFTER REGULAR USE AS DIRECTED
- EXCESSIVE IRRITATION OCCURS

KEEP OUT OF REACH OF CHILDREN

- IF SWALLOWED, GET MEDICAL HELP OR CONTACT A POISON CONTROL CENTER RIGHT AWAY
- TO PREVENT STAINING DO NOT USE IN PLASTIC OR FIBERGLASS TUBS, SINKS OR BASINS. CUTAR MAY STAIN LIGHT COLORED FABRICS

DIRECTIONS

- APPLY TO AFFECTED AREAS ONE TO FOUR TIMES DAILY OR AS DIRECTED BY A DOCTOR
- AS A MEDICATED LOTION: GENTLY RUB A SMALL AMOUNT ONTO AFFECTED AREAS. BLOT OFF EXCESS WITH A TISSUE TO HELP PREVENT STAINING OF CLOTHING OR LINENS
- IN THE BATH: POUR A LIBERAL QUANTITY (2 TO 4 OZ.) INTO THE TUB, MAKING SURE CUTAR IS WELL MIXED. SOAK FOR 10 TO 20 MINUTES, OR AS DIRECTED BY YOUR DOCTOR. AFTER TREATMENT, PAT SKIN DRY.
- GUARD AGAINST SLIPPING.
- AS A HAND OR FOOT SOAK: ADD 1 TO 2 OZ. TO A SINK OR BASIN. MIX WELL AND SOAK FOR 5 TO 10 MINUTES OR AS DIRECTED BY YOUR DOCTOR.

INACTIVE INGREDIENTS

WATER, MINERAL OIL, ISOPROPYL MYRISTATE, POLYSORBATE 80, SORBITAN SESQUIOLEATE, LANOLIN ALCOHOLS EXTRACT, METHYL AND PROPYL PARABENS, FRAGRANCE, XANTHAN GUM, CARBOMER